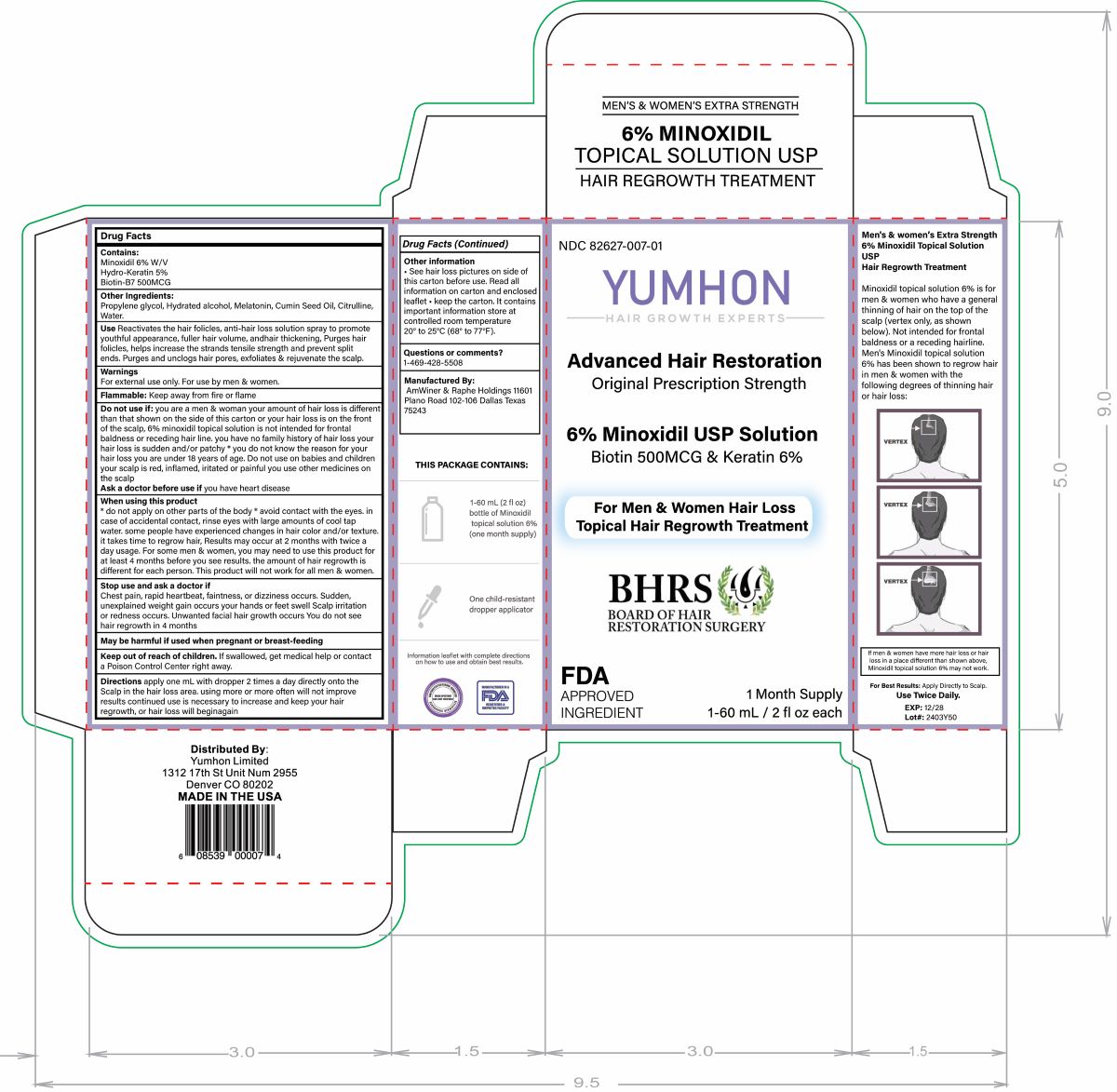 DRUG LABEL: YUMHON 6% MINOXIDIL
NDC: 82627-007 | Form: LIQUID
Manufacturer: AmWiner & Raphe Holdings
Category: otc | Type: HUMAN OTC DRUG LABEL
Date: 20240728

ACTIVE INGREDIENTS: MINOXIDIL 6 g/100 mL
INACTIVE INGREDIENTS: BIOTIN 0.05 g/100 mL; MELATONIN 2 g/100 mL; DIPROPYLENE GLYCOL 34 g/100 mL; HAIR KERATIN AMINO ACIDS 5 g/100 mL; CITRULLINE 2 g/100 mL; WATER 20.95 g/100 mL; ALCOHOL 30 g/100 mL

PACKAGE LABEL

Contains: Minoxidil 6%, Hydrolyzed Keratin 5%, and Biotin 500mcg

Purpose: Anti-hair loss

Other Ingredients: Propylene glycol, Hydrated alcohol, Cumin Seed Oil, Citrulline, Water.

Use: Reactivates the hair follicles, anti-hair loss solution spray to promote a youthful appearance, hair volume, and hair thickening. Purges hair follicles, help increase the strand's tensile strength and prevents split ends. Purges, exfoliates & rejuvenates the scalp.

Directions: Apply one ml with a dropper two times a day directly onto the desired area.

Warning: For External use only!, keep away from fire and flame.

Other Information: Store at room temperature e 20° to 25°C (68° to 77°F).

Comments or Questions Contact:1-469-428-5508

Distributed By: Yumhon Limited

Room 301, Qianhai Yigang Center, Qianhai Comprehensive Bonded Zone, Nanshan, Shenzhen

Phone: 8618576787419

email: cyy@ccbgl.com